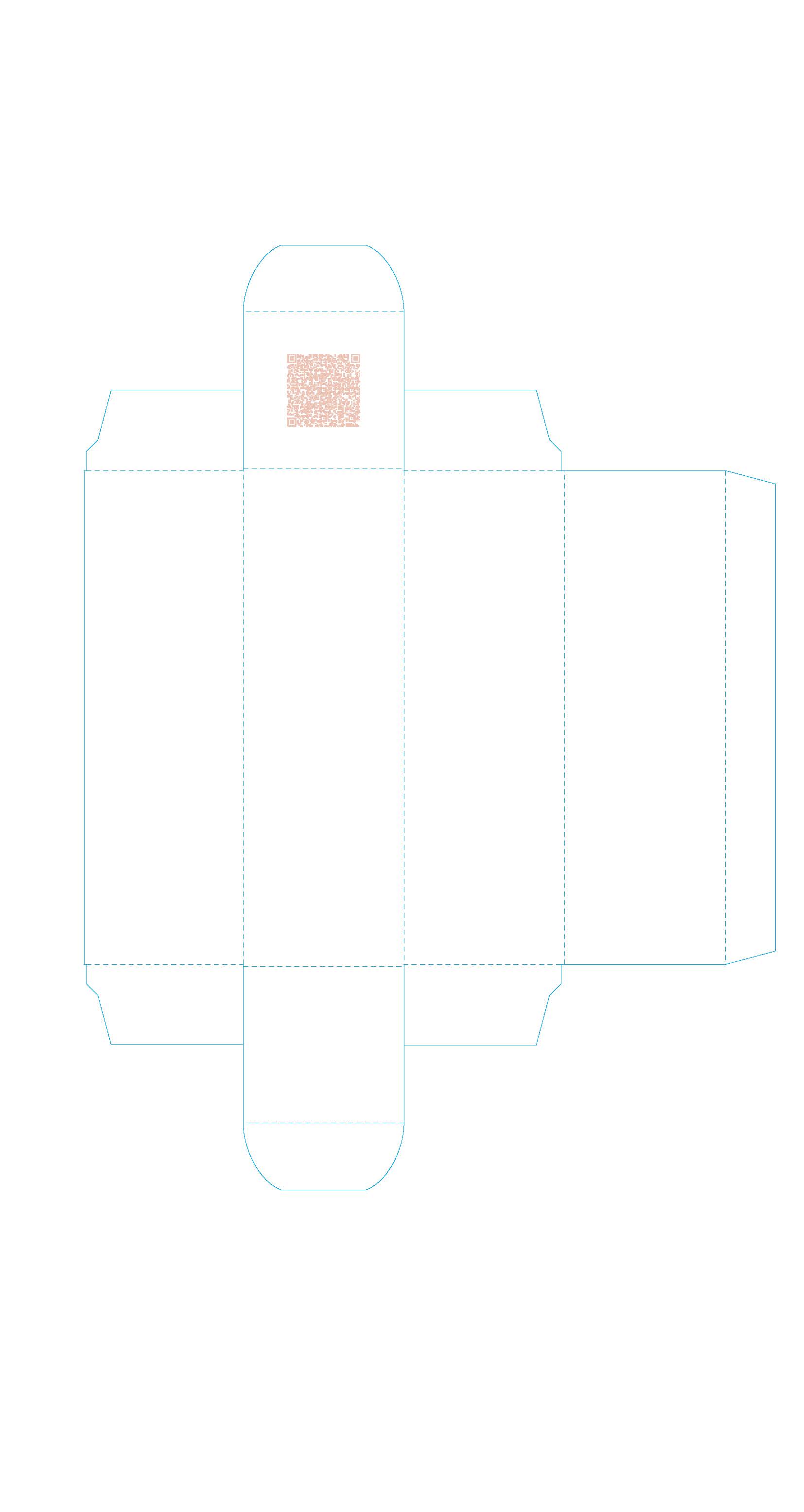 DRUG LABEL: Sunsolve MD Mineral Shade Quartz 001
NDC: 84878-401 | Form: LOTION
Manufacturer: Sunsolve MD Inc
Category: otc | Type: HUMAN OTC DRUG LABEL
Date: 20251114

ACTIVE INGREDIENTS: ZINC OXIDE 132 mg/1 mL
INACTIVE INGREDIENTS: PALMITOYL TETRAPEPTIDE-7; TRILAURETH-4 PHOSPHATE; BUTYLOCTYL SALICYLATE; OCTYLDODECYL NEOPENTANOATE; .ALPHA.-BISABOLOL, (+)-; BUTYLENE GLYCOL; POLYSORBATE 20; SODIUM HYDROXIDE; WATER; ISODODECANE; NIACINAMIDE; ETHYLHEXYLGLYCERIN; HEXYLENE GLYCOL; GLYCERIN; DIMETHICONOL/PROPYLSILSESQUIOXANE/SILICATE CROSSPOLYMER (450000000 MW); PROPANEDIOL; TETRASODIUM GLUTAMATE DIACETATE; CARRAGEENAN; SODIUM CHLORIDE; PHENOXYETHANOL; PALMITOYL TRIPEPTIDE-1; .BETA.-TOCOPHEROL; POLYMETHYLSILSESQUIOXANE (4.5 MICRONS)

Sunsolve MD Mineral Shade Quartz 001